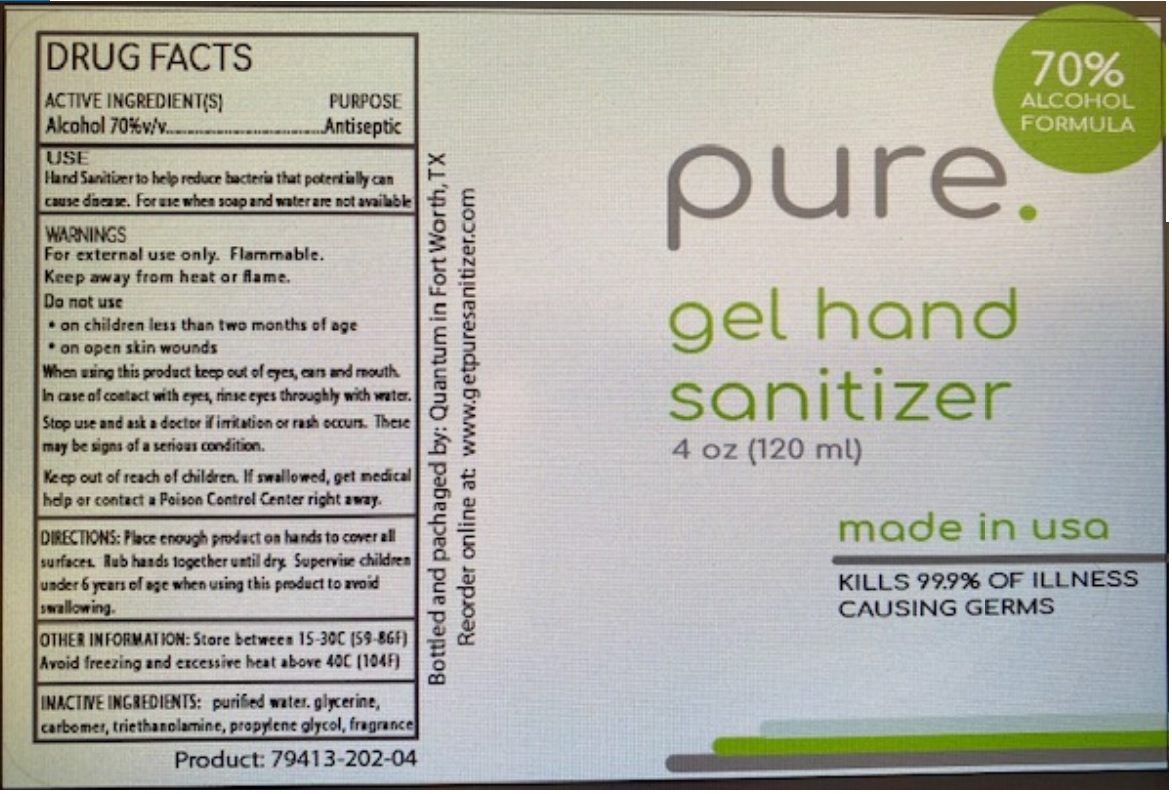 DRUG LABEL: Quantum Gel Hand Sanitizer
NDC: 79413-202 | Form: GEL
Manufacturer: Quantum Valve And Oilfield Solutions, Llc
Category: otc | Type: HUMAN OTC DRUG LABEL
Date: 20200728

ACTIVE INGREDIENTS: ALCOHOL 70 mL/100 mL
INACTIVE INGREDIENTS: WATER; GLYCERIN; CARBOMER HOMOPOLYMER, UNSPECIFIED TYPE; TROLAMINE; PROPYLENE GLYCOL

pure. gel hand sanitizer

ACTIVE INGREDIENTS(S)

Alcohol 70%v/v

PURPOSE

Antiseptic

USE

Hand sanitizer to help reduce bacteria that potentially can cause disease. For use when soap and water are not available

WARNINGS

For external use only. Flammable.

Keep away from heat or flame.

Do not use

• on children less than two months of age

• on open skin wounds

When using this product keep out of eyes, ears and mouth.

In case of contact with eyes, rinse eyes thoroughly with water.

Stop use and ask a doctor if irritation or rash occurs. These may be signs of a serious condition.

Keep out of reach of children. If swallowed, get medical help or contact a Poison Control Center right away.

DOSAGE AND ADMINISTRATION

DIRECTIONS: Place enough product on hands to cover all surfaces. Rub hands together until dry. Supervise children under 6 years of age when using this product to avoid swallowing.

OTHER INFORMATION: Store between 15-30C (59-86F)

Avoid freezing and excessive heat above 40C (104F)

INACTIVE INGREDIENT

INACTIVE INGREDIENTS: purified water, glycerine, carbomer, triethanolamine, propylene glycol, fragrance

70% ALCOHOL FORMULA

made in usa

KILLS 99.9% OF ILLNESS CAUSING GERMS

Bottled and packaged by: Quantum in Fort Worth, TX

Reorder online at: www.getpuresanitizer.com